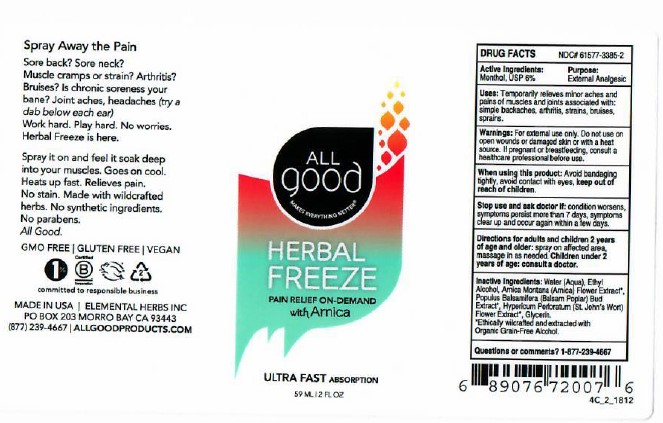 DRUG LABEL: HERBAL FREEZE
NDC: 61577-3385 | Form: SPRAY
Manufacturer: SOMBRA COSMETICS INC.
Category: otc | Type: HUMAN OTC DRUG LABEL
Date: 20230308

ACTIVE INGREDIENTS: MENTHOL 0.06 g/1 g
INACTIVE INGREDIENTS: WATER; ALCOHOL; ARNICA MONTANA FLOWER; POPULUS BALSAMIFERA LEAF BUD; HYPERICUM PERFORATUM FLOWER; GLYCERIN

Herbal Freeze Pain Relieving Gel

Active Ingredients

Menthol USP %

Purpose

External Analgesic

Keep out of reach of children

Uses

Temporarily relieves minor aches and pains of muscles and joints associated with: arthritis, simple backaches, strains, bruises, and sprains

Warnings

For external use only. Do not use on wounds or damaged skin or with a heat source. If pregnant or breastfeeding, consult a healthcare professional before use.When using this product: avoid bandaging tightly, avoid contact with eyes, keep out of reach of children.

Stop use and ask doctor if: condition worsens, symptoms persist for more than 7 days, symptoms clear up and occur again within a few days.

Directions

adults and children 2 years of age and older: apply to affected area not more than 3 to 4 times daily, rub in thoroughly until gel is absorbed, children under 2 years of age: consult a doctor.

Inactive Ingredients

Purified Water, Ethyl Alcohol, Arnica Montana (Arnica) Flower Extract, Populus Balsimafora (Balsam Poplar) Bud Extract, Hypericum Perforatum (St. John's Wort) Flower Extract, Glycerin

Questions or Comments

1-877-239-4667